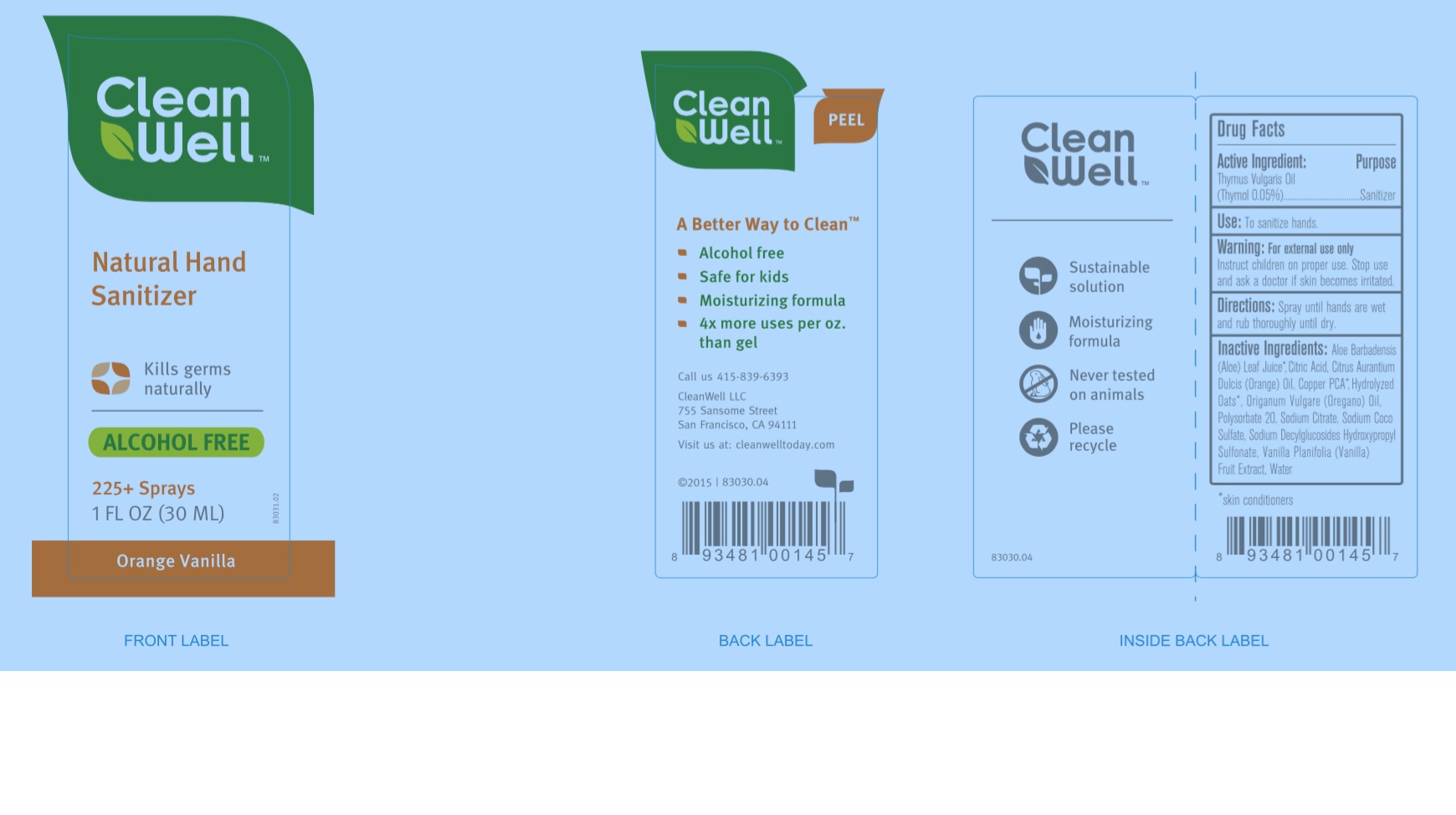 DRUG LABEL: CleanWell Natural Orange Vanilla Hand Sanitizer
NDC: 28107-008 | Form: SPRAY
Manufacturer: CleanWell, LLC
Category: otc | Type: HUMAN OTC DRUG LABEL
Date: 20180404

ACTIVE INGREDIENTS: THYMOL 0.0005 kg/1 kg
INACTIVE INGREDIENTS: THYME OIL 0.0003 kg/1 kg; OREGANO LEAF OIL 0.0001 kg/1 kg; ORANGE OIL 0.0019 kg/1 kg; DECANAL 0.00015 kg/1 kg; VANILLA PLANIFOLIA OIL 0.002 kg/1 kg; SODIUM DECYLGLUCOSIDES HYDROXYPROPYLSULFONATE 0.0016 kg/1 kg; SODIUM COCO-SULFATE 0.0032 kg/1 kg; ANHYDROUS CITRIC ACID 0.00046 kg/1 kg; SODIUM CITRATE 0.0007 kg/1 kg; COPPER 0.0008 kg/1 kg; AMINO ACIDS, OAT 0.001 kg/1 kg; ALOE VERA LEAF 0.0025 kg/1 kg; WATER 0.98525 kg/1 kg

CleanWell Natural Orange Vanilla Hand Sanitizer

Active Ingredient:

Thymus Vulgaris Oil (Thymol 0.05%)

Purpose

Sanitizer

Use:

To sanitize hands

Warning:

For external use only

Instruct children on proper use.

Stop use and ask a dotor if skin becomes irritated.

Directions:

Spray until hands are wet and rub thoroughly until dry.

Inactive Ingredients:

Aloe Barbadensis (Aloe) Leaf Juice*, Citric Acid, Citrus Aurantium Dulcis (Orange) Oil, Copper PCA*, Hydrolyzed Oats*, Origanum Vulgare (Oregano) Oil, Sodium Citrate, Sodium Coco Sulfate, Sodium Decylglucosides Hydroxypropyl Sulfonate, Vanilla Planifolia (Vanilla) Fruit Extract, Water